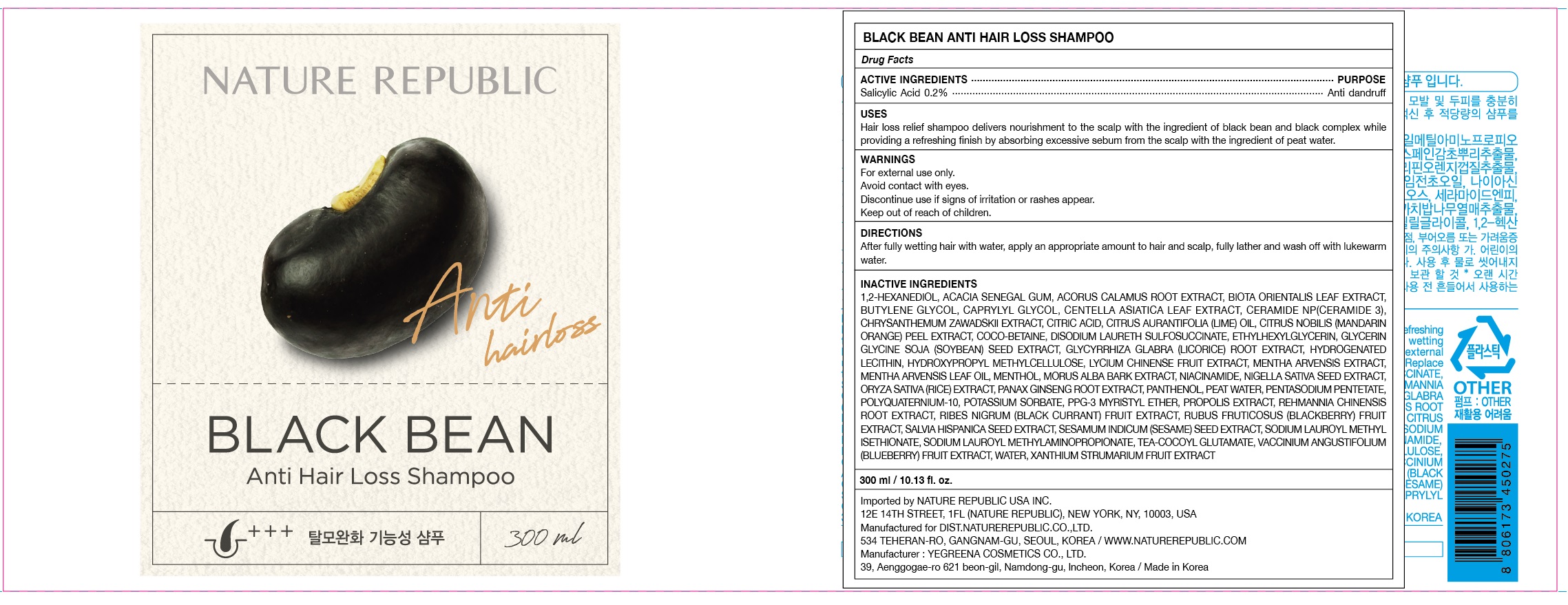 DRUG LABEL: BLACK BEAN ANTI HAIR LOSS
NDC: 51346-514 | Form: SHAMPOO
Manufacturer: NATURE REPUBLIC CO., LTD.
Category: otc | Type: HUMAN OTC DRUG LABEL
Date: 20201029

ACTIVE INGREDIENTS: Salicylic Acid 0.6 g/300 mL
INACTIVE INGREDIENTS: 1,2-Hexanediol; ACACIA

ACTIVE INGREDIENT

Salicylic Acid 0.2%

INACTIVE INGREDIENTS

1,2-Hexanediol, Acacia Senegal Gum, Acorus Calamus Root Extract, Biota Orientalis Leaf Extract, Butylene Glycol, Caprylyl Glycol, Centella Asiatica Leaf Extract, Ceramide NP(Ceramide 3), Chrysanthemum Zawadskii Extract, Citric acid, Citrus Aurantifolia (Lime) Oil, Citrus Nobilis (Mandarin Orange) Peel Extract, Coco-Betaine, Disodium Laureth Sulfosuccinate, Ethylhexylglycerin, Glycerin Glycine Soja (Soybean) Seed Extract, Glycyrrhiza Glabra (Licorice) Root Extract, Hydrogenated Lecithin, Hydroxypropyl Methylcellulose, Lycium Chinense Fruit Extract, Mentha Arvensis Extract, Mentha Arvensis Leaf Oil, Menthol, Morus Alba Bark Extract, Niacinamide, Nigella Sativa Seed Extract, Oryza Sativa (Rice) Extract, Panax Ginseng Root Extract, Panthenol, Peat water, Pentasodium Pentetate, Polyquaternium-10, Potassium sorbate, PPG-3 Myristyl Ether, Propolis Extract, Rehmannia Chinensis Root Extract, Ribes Nigrum (Black Currant) Fruit Extract, Rubus Fruticosus (Blackberry) Fruit Extract, Salvia Hispanica Seed Extract, Sesamum Indicum (Sesame) Seed Extract, Sodium Lauroyl Methyl Isethionate, Sodium Lauroyl Methylaminopropionate, TEA-Cocoyl Glutamate, Vaccinium Angustifolium (Blueberry) Fruit Extract, Water, Xanthium Strumarium Fruit Extract

PURPOSE

Anti dandruff

WARNINGS

For external use only.
Avoid contact with eyes.
Discontinue use if signs of irritation or rashes appear.
Keep out of reach of children.

KEEP OUT OF REACH OF CHILDREN

Uses

Hair loss relief shampoo delivers nourishment to the scalp with the ingredient of black bean and black complex while providing a refreshing finish by absorbing excessive sebum from the scalp with the ingredient of peat water.

Directions

After fully wetting hair with water, apply an appropriate amount to hair and scalp, fully lather and wash off with lukewarm water.